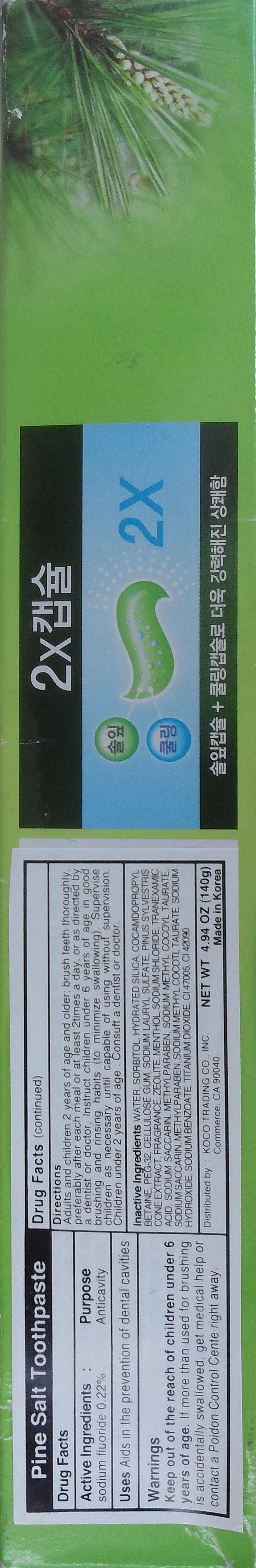 DRUG LABEL: PINE SALT 140g
NDC: 69642-1200 | Form: PASTE, DENTIFRICE
Manufacturer: HANUL TRADING CO., LTD.
Category: otc | Type: HUMAN OTC DRUG LABEL
Date: 20191224

ACTIVE INGREDIENTS: SODIUM FLUORIDE 0.308 g/140 g
INACTIVE INGREDIENTS: WATER; SORBITOL

ACTIVE INGREDIENT

Active Ingredient: SODIUM FLUORIDE (0.22%)

INACTIVE INGREDIENT

Inactive Ingredients: WATER, SORBITOL, HYDRATED SILICA, COCAMDOPROPYL BETAINE, PEG-32, CELLULOSE GUM, SODIUM LAURYL SULFATE, PINUS SYLVESTRIS CONE EXTRACT, FRAGRANCE, ZEOLITE, MENTHOL, SODIUM CHLORIDE, TRANEXAMIC ACID, SODIUM SACCARIN, METHYLPARABEN, SODIUM METHYL COCOYL TAURATE, SODIUM HYDROXIDE, SODIUM BENZOATE, TITANIUM DIOXIDE, CI 47005, CI 42090

PURPOSE

Purpose: Anticavity

WARNINGS

Warnings: Keep out of the reach of children under 6 years of age. If more than used for brushing is accidentally swallowed, get medical help or contact a Poison Control Center right away.

KEEP OUT OF REACH OF CHILDREN

Keep out of the reach of children under 6 years of age.

USE

USE: Aids in the prevention of dental cavities

Directions

Directions: Adults and children 2 years of age and older; brush teeth thoroughly, preferably after each meal or at least 2 times a day, or as directed by a dentist or doctor. Instruct children under 6 years of age in good brushing and rinsing habits (to minimize swallowing). Supervise children as necessary until capable of using without supervision. Children under 2 years of age: Consult a dentist or doctor.